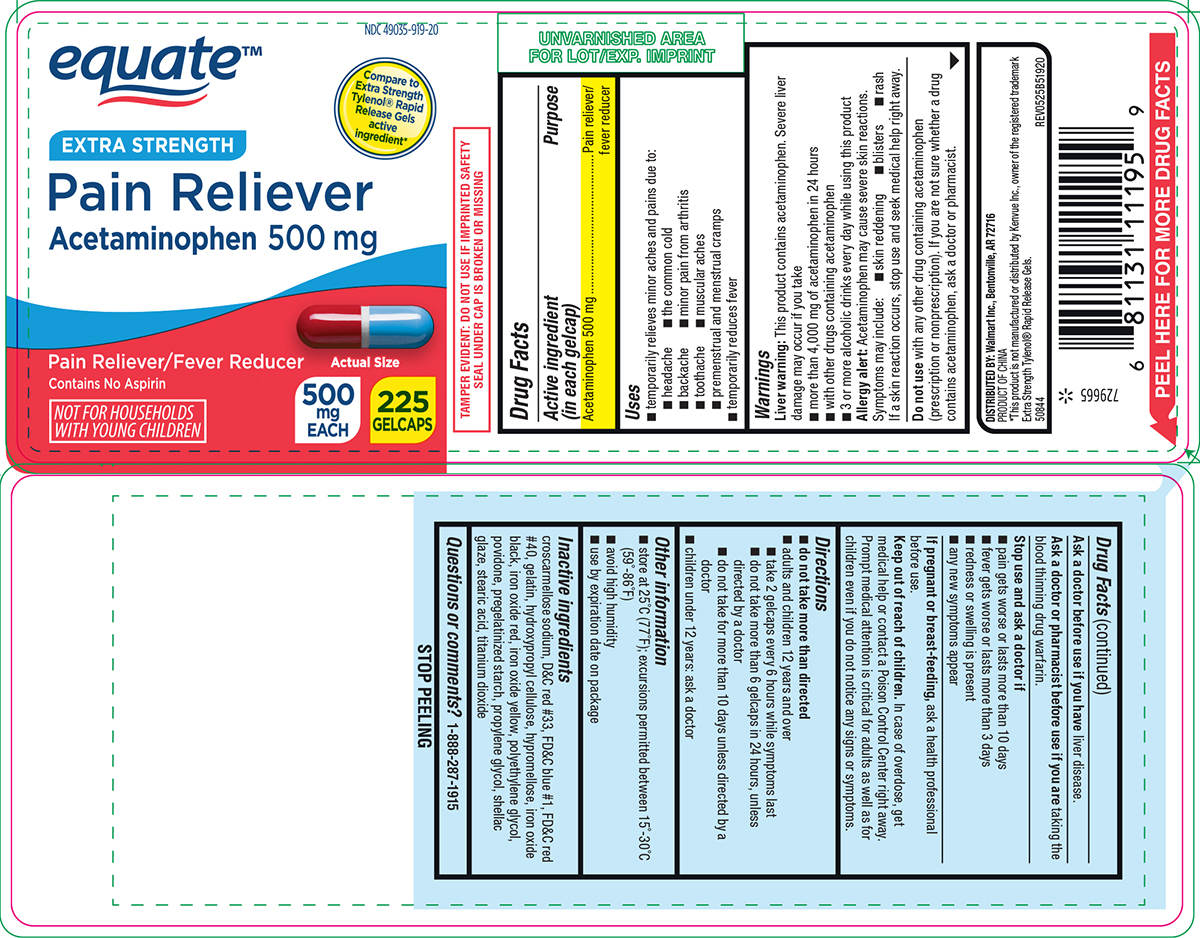 DRUG LABEL: Pain Reliever
NDC: 49035-919 | Form: TABLET, COATED
Manufacturer: Wal-Mart Stores Inc
Category: otc | Type: HUMAN OTC DRUG LABEL
Date: 20260202

ACTIVE INGREDIENTS: ACETAMINOPHEN 500 mg/1 1
INACTIVE INGREDIENTS: CROSCARMELLOSE SODIUM; D&C RED NO. 33; FD&C BLUE NO. 1; FD&C RED NO. 40; GELATIN, UNSPECIFIED; HYDROXYPROPYL CELLULOSE, UNSPECIFIED; HYPROMELLOSE, UNSPECIFIED; FERROSOFERRIC OXIDE; FERRIC OXIDE RED; FERRIC OXIDE YELLOW; POLYETHYLENE GLYCOL, UNSPECIFIED; POVIDONE, UNSPECIFIED; STARCH, CORN; PROPYLENE GLYCOL; SHELLAC; STEARIC ACID; TITANIUM DIOXIDE

Equate 44-519-Pain Reliever

Active ingredient (in each gelcap)

Acetaminophen 500 mg

Purpose

Pain reliever/fever reducer

Uses

- temporarily relieves minor aches and pains due to:
  - the common cold
  - minor pain from arthritis
  - muscular aches
  - toothache
  - backache
  - premenstrual and menstrual cramps
  - headache
- temporarily reduces fever

Warnings

Liver warning: This product contains acetaminophen. Severe liver damage may occur if you take

- more than 4,000 mg of acetaminophen in 24 hours
- with other drugs containing acetaminophen
- 3 or more alcoholic drinks every day while using this product

Allergy alert: Acetaminophen may cause severe skin reactions. Symptoms may include:

- blisters
- rash
- skin reddening

If a skin reaction occurs, stop use and seek medical help right away.

Do not use

with any other drug containing acetaminophen (prescription or nonprescription). If you are not sure whether a drug contains acetaminophen, ask a doctor or pharmacist.

Ask a doctor before use if you have

liver disease.

Ask a doctor or pharmacist before use if you are

taking the blood thinning drug warfarin.

Stop use and ask a doctor if

- any new symptoms appear
- pain gets worse or lasts more than 10 days
- fever gets worse or lasts more than 3 days
- redness or swelling is present

If pregnant or breast-feeding,

ask a health professional before use.

Keep out of reach of children.

In case of overdose, get medical help or contact a Poison Control Center right away. Prompt medical attention is critical for adults as well as for children even if you do not notice any signs or symptoms.

Directions

- do not take more than directed
- adults and children 12 years and over
  - take 2 gelcaps every 6 hours while symptoms last
  - do not take more than 6 gelcaps in 24 hours, unless directed by a doctor
  - do not take for more than 10 days unless directed by a doctor
- children under 12 years: ask a doctor

Other information

- store at 25°C (77°F); excursions permitted between 15°-30°C (59°-86°F)
- avoid high humidity
- use by expiration date on package

Inactive ingredients

croscarmellose sodium, D&C red #33, FD&C blue #1, FD&C red #40, gelatin, hydroxypropyl cellulose, hypromellose, iron oxide black, iron oxide red, iron oxide yellow, polyethylene glycol, povidone, pregelatinized starch, propylene glycol, shellac glaze, stearic acid, titanium dioxide

Questions or comments?

1-888-287-1915

Principal Display Panel

equate™

NDC 49035-919-20

Compare to
Extra Strength
Tylenol® Rapid
Release Gels
active
ingredient*

EXTRA STRENGTH
Pain Reliever
Acetaminophen 500 mg

Pain Reliever/Fever Reducer
Contains No Aspirin

NOT FOR HOUSEHOLDS
WITH YOUNG CHILDREN

Actual Size

500
mg
EACH

225
GELCAPS

Actual Size

TAMPER EVIDENT: DO NOT USE IF IMPRINTED SAFETY
SEAL UNDER CAP IS BROKEN OR MISSING

DISTRIBUTED BY: Walmart Inc., Bentonville, AR 72716
PRODUCT OF CHINA
*This product is not manufactured or distributed by Kenvue Inc., owner of the registered trademark
Extra Strength Tylenol® Rapid Release Gels.
50844 REV0525B51920

Equate 44-519